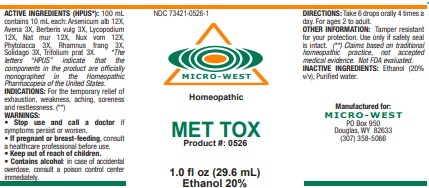 DRUG LABEL: MET TOX
NDC: 73421-0526 | Form: LIQUID
Manufacturer: White Manufacturing Inc. DBA Micro-West
Category: homeopathic | Type: HUMAN OTC DRUG LABEL
Date: 20221202

ACTIVE INGREDIENTS: ARSENIC TRIOXIDE 12 [hp_X]/29.6 mL; AVENA SATIVA FLOWERING TOP 3 [hp_X]/29.6 mL; BERBERIS VULGARIS ROOT BARK 3 [hp_X]/29.6 mL; LYCOPODIUM CLAVATUM SPORE 12 [hp_X]/29.6 mL; SODIUM CHLORIDE 12 [hp_X]/29.6 mL; STRYCHNOS NUX-VOMICA SEED 12 [hp_X]/29.6 mL; PHYTOLACCA AMERICANA ROOT 3 [hp_X]/29.6 mL; FRANGULA ALNUS BARK 3 [hp_X]/29.6 mL; SOLIDAGO VIRGAUREA FLOWERING TOP 3 [hp_X]/29.6 mL; TRIFOLIUM PRATENSE FLOWER 3 [hp_X]/29.6 mL
INACTIVE INGREDIENTS: ALCOHOL; WATER

MET TOX

ACTIVE INGREDIENT

ACTIVE INGREDIENTS (HPUS*): 100 mL contains 10 mL each: Arsenicum alb 12X, Avena 3X, Berberis vulg 3X, Lycopodium
12X, Nat mur 12X, Nux vom 12X, Phytolacca 3X, Rhamnus frang 3X, Solidago 3X, Trifolium prat 3X.

*The letters “HPUS” indicate that the components in the product are officially monographed in the Homeopathic Pharmacopeia of the United States.

(**) Claims based on traditional homeopathic practice, not accepted medical evidence. Not FDA evaluated.

INDICATIONS AND USAGE

INDICATIONS: For the temporary relief of exhaustion, weakness, aching, soreness and restlessness. (**)

WARNINGS:
• Stop use and call a doctor if symptoms persist or worsen.
• If pregnant or breast-feeding, consult a healthcare professional before use.
• Keep out of reach of children.
• Contains alcohol: in case of accidental overdose, consult a poison control center immediately.

• Keep out of reach of children.

DOSAGE AND ADMINISTRATION

DIRECTIONS: Take 6 drops orally 4 times a day. For ages 2 to adult.

OTHER INFORMATION: Tamper resistant for your protection. Use only if safety seal is intact.

INACTIVE INGREDIENTS: Ethanol (20% v/v), Purified w

QUESTIONS

Manufactured for:

MICRO-WEST

PO Box 950 Douglas, WY 82633
(307) 358-5066

PACKAGE LABEL

NDC 73421-0526-1

MICRO-WEST

Homeopathic

MET TOX

Product #: 0526

1.0 fl oz (29.6 mL)

Ethanol 20%

PURPOSE

For the temporary relief of exhaustion, weakness, aching, soreness and restlessness.